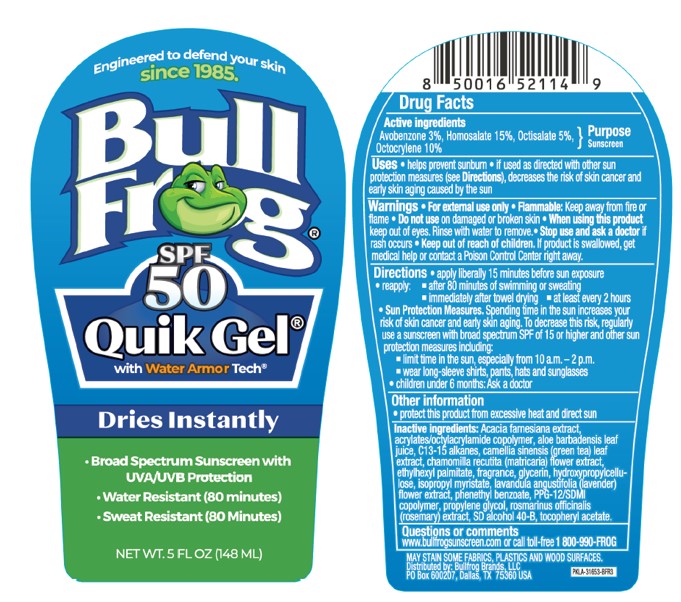 DRUG LABEL: Bull Frog SPF 50
NDC: 77714-002 | Form: GEL
Manufacturer: Bullfrog Brands, LLC
Category: otc | Type: HUMAN OTC DRUG LABEL
Date: 20231113

ACTIVE INGREDIENTS: AVOBENZONE 3 g/100 mL; HOMOSALATE 15 g/100 mL; OCTISALATE 5 g/100 mL; OCTOCRYLENE 10 g/100 mL
INACTIVE INGREDIENTS: ALCOHOL; ALOE VERA LEAF; GREEN TEA LEAF; ACRYLATE/ISOBUTYL METHACRYLATE/N-TERT-OCTYLACRYLAMIDE COPOLYMER (75000 MW); GLYCERIN; CHAMOMILE; VACHELLIA FARNESIANA FLOWER; .ALPHA.-TOCOPHEROL ACETATE; ISOPROPYL MYRISTATE; LAVANDULA ANGUSTIFOLIA SUBSP. ANGUSTIFOLIA FLOWER; PHENETHYL BENZOATE; PROPYLENE GLYCOL; C13-15 ALKANE; ETHYLHEXYL PALMITATE; HYDROXYPROPYL CELLULOSE, UNSPECIFIED; PPG-12/SMDI COPOLYMER; ROSEMARY; WATER

Bull Frog SPF50 Quik Gel with water Armour Tech

Active Ingredient

Avobenzone 3%
Homosalate 15%
Octisalate 5%
Octocrylene 10%

Purpose

Sunscreen

Uses

• helps prevent sunburn • if used as directed with other sun protection measures (see Directions) decreases the risk of skin cancer and early skin aging caused by the sun.

Warnings

For external use only

Flammable: Keep away from fire or flame.

Do not use

on damaged or broken skin.

When using this product

keep out of eyes. Rinse with water to remove.

Stop use and ask a doctor

if rash occurs

Keep out of reach of children.

If product is swallowed, get medical help or contact a Poison Control Center right away.

Directions

• Apply liberally 15 minutes before sun exposure

• Reapply:

• after 80 minutes of swimming or sweating

• immediately after towel drying

• at least every 2 hours.

• Sun Protection Measures. Spending time in the sun increases your risk of skin cancer and early skin aging. To decrease this risk, regularly use a sunscreen with a Broad Spectrum SPF value of 15 or higher and other sun protection measures including:

• limit time in the sun, especially from 10 a.m.-2 p.m.

• wear long-sleeved shirts, pants, hats, and sunglasses.

• Children under 6 months of age: Ask a doctor.

Other information

- protect the product in this container from excessive heat and direct sun

Inactive Ingredients

Acacia Famesiana extract, acrylate/octyl acrylamide copolymer, aloe barbadensis leaf extract, C13-15 alkanes, camellia sinensis (green tea) leaf extract, chamomile recutita (matricaria) flower extract, cyclohexasiloxane, ethylhexyl palmitate, fragrance, glycerin, hydroxypropycellulose, isopropyl myrsitate, lavandula angustifolia (lavender) flower extract, phenethyl benzoate, PPG-12/SDMI copolymer, propylene glycol, rosmarinus officinalis (rosemary) extract, SD alcohol 40-B, tocopheryl acetate.